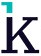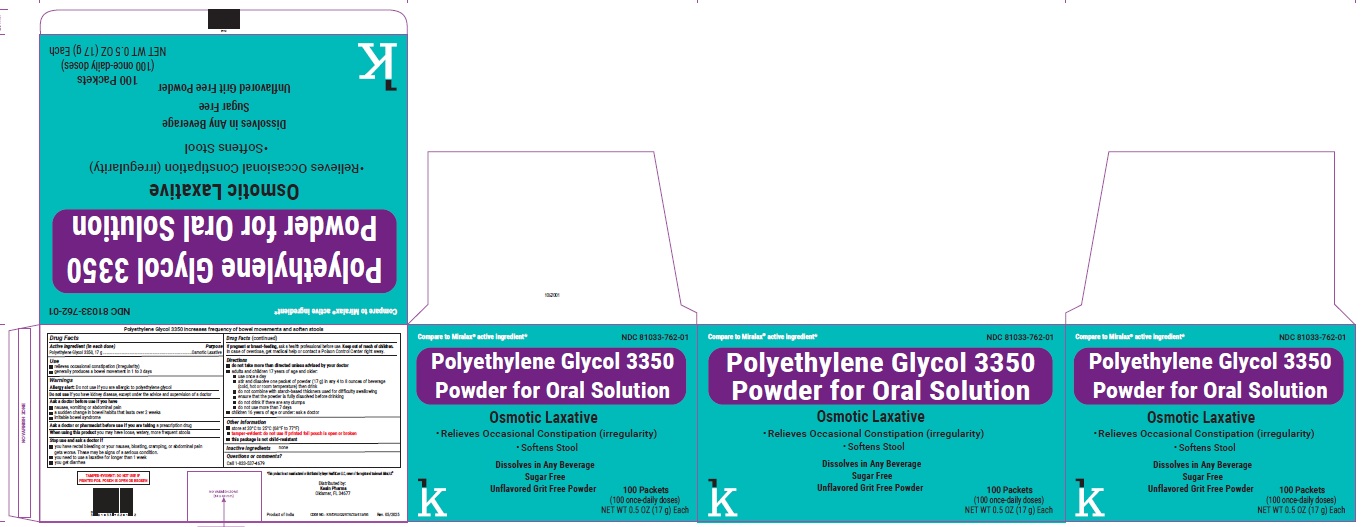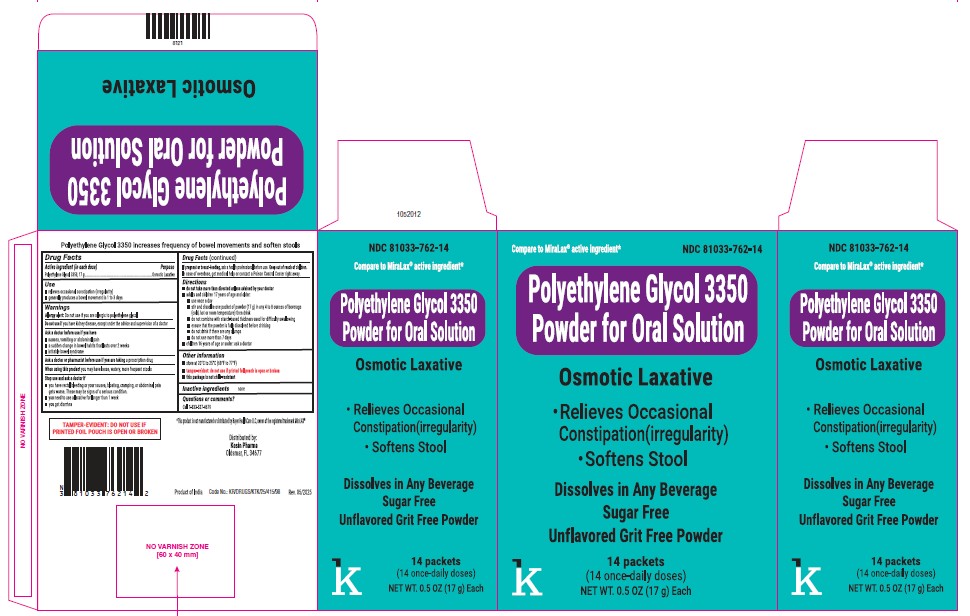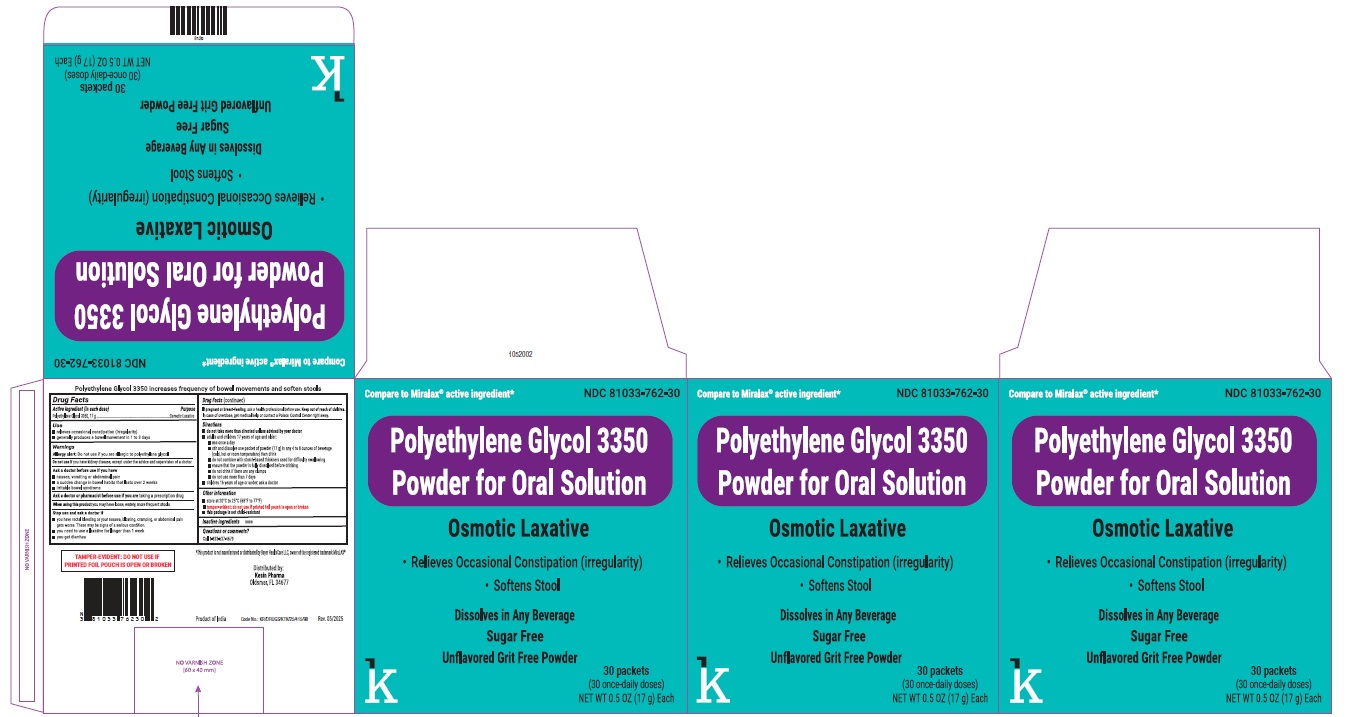 DRUG LABEL: Polyethylene Glycol 3350
NDC: 81033-762 | Form: POWDER, FOR SOLUTION
Manufacturer: Kesin Pharma Corporation
Category: otc | Type: HUMAN OTC DRUG LABEL
Date: 20250612

ACTIVE INGREDIENTS: POLYETHYLENE GLYCOL 3350 17 g/17 g

Polyethelene Glycol 3350 Powder for OralSolution

Polyethylene Glycol 3350 increases frequency of bowel movements and softens stools

Drug Facts

Active ingredient (in each dose)

Polyethlene Glycol 3350, 17 g

Purpose

Osmotic Laxative

Use

- relieves occasional constipation (irregularity)
- generally produces a bowel movement in 1 to 3 days

Warnings

Allergy alert:

Do not use if you are allergic to polyethylene glycol

Do not use

if you have kidney disease, except under the advice and supervision of a doctor

Ask a doctor before use if you have

- nausea, vomiting or abdominal pain
- a sudden change in bowel habits that lasts over 2 weeks
- irritable bowel syndrome

Ask a doctor or pharmacist before use if you are taking

a prescription drug

When using this product

you may have loose, watery, more frequent stools

Stop use and ask a doctor if

- you have rectal bleeding or your nausea, bloating, cramping or abdominal pain gets worse. These may be signs of a serious condition.
- you need to use a laxative for longer than 1 week
- you get diarrhea

If pregnant or breast-feeding,

ask a health professional before use.

Keep out of the reach of children.

OVERDOSAGE

In case of overdose, get medical help or contact a Poison Control Center right away.

Directions

- do not take more than directed unless advised by your doctor
- adults and children 17 yearsof age and older:
- use once a day
- stir and dissolve one packet of powder (17 g) in any 4 to 8 ounce of beverage (cold, hot or room temperature) then drink
- do not combine with starch-based thickners used for difficulty swallowing
- ensure that the powder is fully dissolved before drinking
- do not drink if there are any clumps
- do not use more than 7 days
- children 16 years of age or under: ask a doctor

Other information

- store at 20°C to 25°C (68°F to 77°F)
- tamper-evident: do not use if printed foil pouch is open or broken
- this package is not child-resistant

Inactive ingredients

none

Questions or comments?

Call 1-833-537-4679

TAMPER-EVIDENT: DO NOT USE IF PRINTED FOIL POUCH IS OPEN OR BROKEN

*This product is not manufactured by Bay HealthCare LLC, owner of the registered trademark MiraLAX®

Distributed by:

Kesin Pharma

Oldsmar, FL 34677

PACKAGE LABEL.PRINCIPAL DISPLAY PANEL

NDC 81033-762-14

Polyethylene Glycol 3350 Powder for Oral Solution

Osmotic Laxative

14 Packets

(14 once-daily-doses)

PACKAGE LABEL.PRINCIPAL DISPLAY PANEL

NDC 81033-762-30

Polyethylene Glycol 3350 Powder for Oral Solution

Osmotic Laxative

30 Packets

(30 once-daily doses)

PACKAGE LABEL.PRINCIPAL DISPLAY PANEL

NDC 81033-762-01

Polyethylene Glycol 3350 Powder for Oral Solution

Osmotic laxative

100 Packets

(100 once-daily doses)